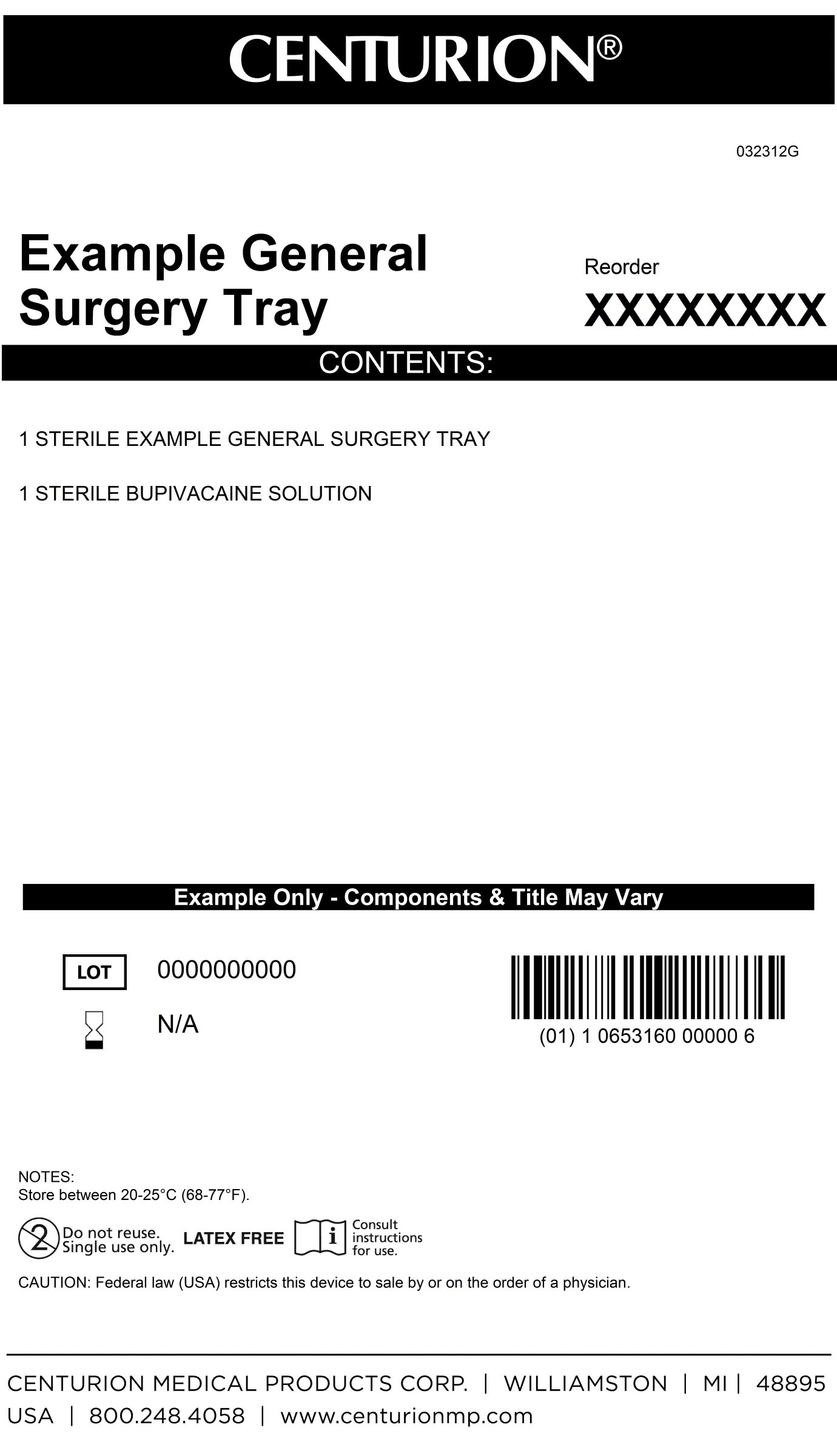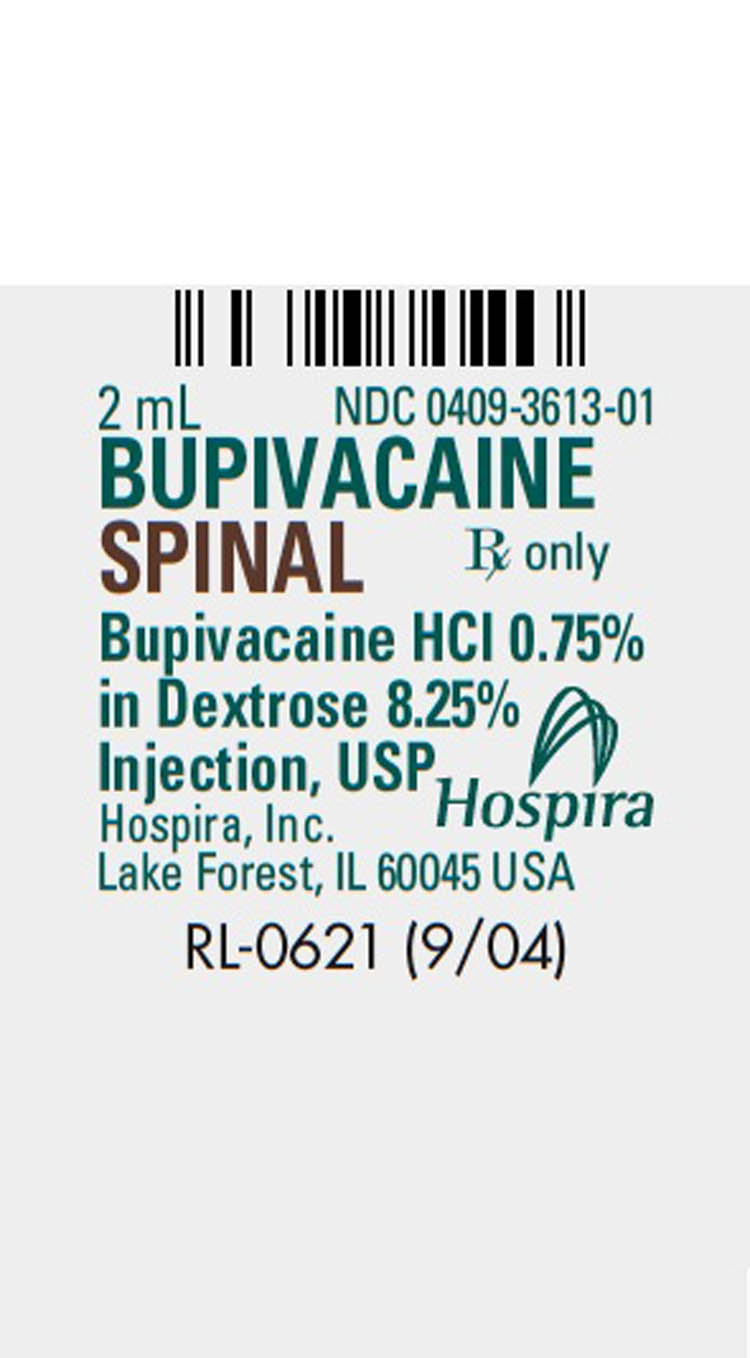 DRUG LABEL: General Surgery Kit
NDC: 24840-1570 | Form: KIT | Route: SUBARACHNOID
Manufacturer: Centurion Medical Products
Category: other | Type: MEDICAL DEVICE
Date: 20120925

ACTIVE INGREDIENTS: BUPIVACAINE HYDROCHLORIDE 7.5 mg/1 mL
INACTIVE INGREDIENTS: SODIUM HYDROXIDE; HYDROCHLORIC ACID; ANHYDROUS DEXTROSE 82.5 mg/1 mL

General Surgery Kit

DESCRIPTION

Bupivacaine hydrochloride is a white crystalline powder that is freely soluable in 95 percent ethanol, soluable in water and slightly soluable in chloroform or acetone. The pH of this solution is 5.5 (4.0 to 6.5) with sodium hydroxide and/or hydrochloric acid. Bupivacaine Hydrochloride is available in sterile, hyperbaric solution for subarachnoid injection. Bupivacaine Spinal does not contain preservatives.

PACKAGE LABEL

MM